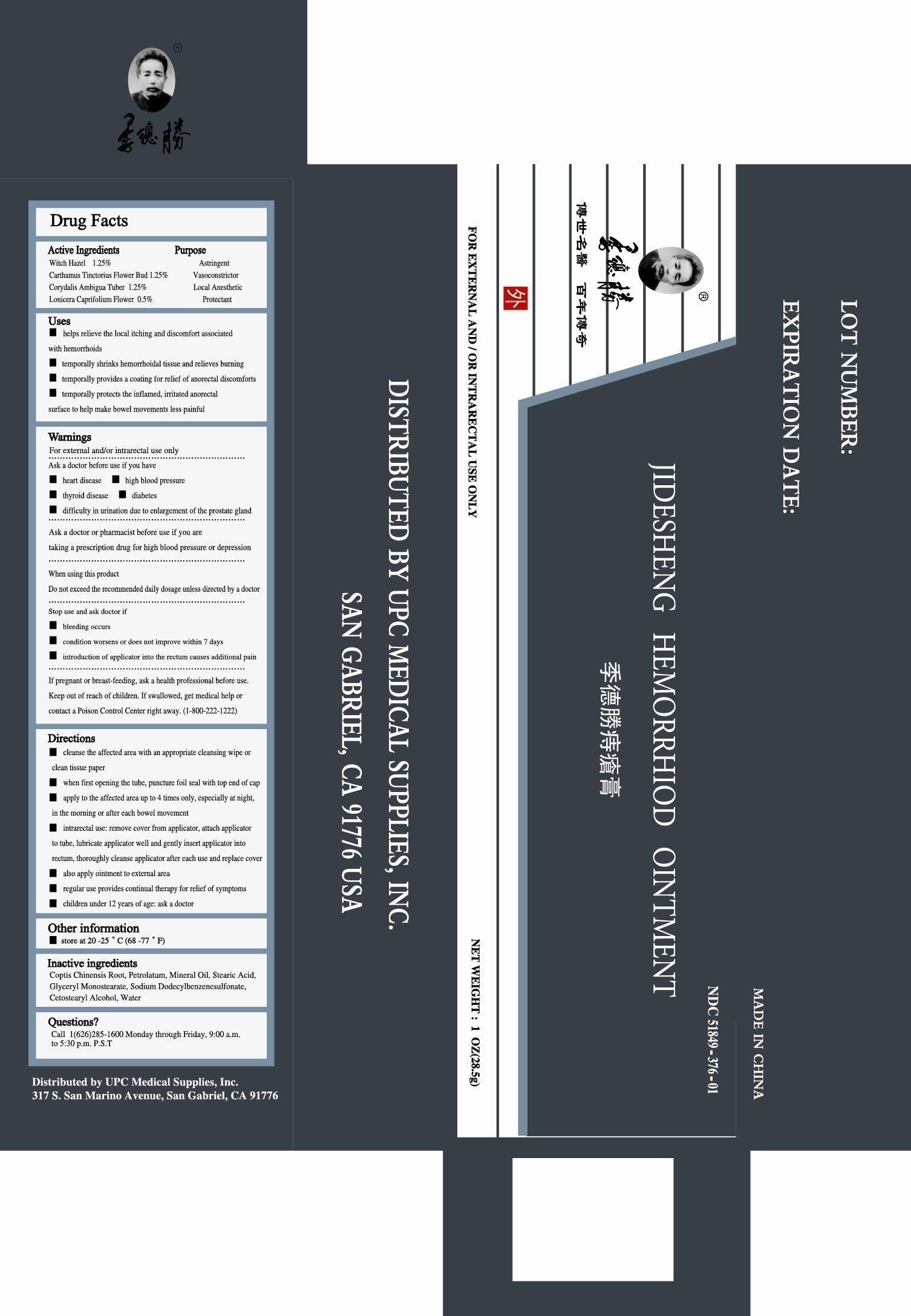 DRUG LABEL: JIDESHENG HEMORRHOID
NDC: 51849-1250 | Form: OINTMENT
Manufacturer: NANTONG JIDESHENG BIOLOGY HEALTH CARE PRODUCTS CO LTD
Category: otc | Type: HUMAN OTC DRUG LABEL
Date: 20130412

ACTIVE INGREDIENTS: WITCH HAZEL 12.5 mg/1000 mg; CARTHAMUS TINCTORIUS FLOWER BUD 12.5 mg/1000 mg; CORYDALIS AMBIGUA TUBER 12.5 mg/1000 mg; LONICERA CAPRIFOLIUM FLOWER 5 mg/1000 mg
INACTIVE INGREDIENTS: COPTIS CHINENSIS ROOT 7.5 mg/1000 mg; PETROLATUM 40 mg/1000 mg; MINERAL OIL 40 mg/1000 mg; STEARIC ACID 55 mg/1000 mg; GLYCERYL MONOSTEARATE 30 mg/1000 mg; SODIUM DODECYLBENZENESULFONATE 10 mg/1000 mg; CETOSTEARYL ALCOHOL 0.4 mg/1000 mg; WATER 744.6 mg/1000 mg

JIDESHENG HEMORRHOID OINTMENT

ACTIVE INGREDIENTS

WITCH HAZEL 1.25%

CARTHAMUS TINCTORIUS FLOWER BUD 1.25%

CORYDALIS AMBIGUA TUBER 1.25%

LONICERA CAPRIFOLIUM FLOWER 0.5%

PURPOSE

ASTRINGENT
VASOCONSTRICTOR
LOCAL ANESTHETIC
PROTECTANT

USES

helps relieve local itching and discomfort associated with hemorrhoids

temporarily shrinks hemorrhoidal tissue and relieves burning

temporarily provides a coating for relief of anorectal dosconforts

temporarily protects the inflamed, irritated anorectal surface to help bowel movements less painful

WARNINGS

For external and/or intrarectal use only

ASK A DOCTOR BEFORE USE IF YOU HAVE

heart disease

high blood pressure

thyroid disease

diabetes

difficulty in urination due to enlargement of the prostate gland

ASK A DOCTOR OR PHARMACIST BEFORE USE IF YOU ARE

presently taking a prescription drug for high blood pressure or depression

WHEN USING THIS PRODUCT

do not exceed the recommended daily dosage unless directed by a doctor

STOP USE AND ASK A DOCTOR IF

bleeding occurs

condition worses or does not improve within 7 days

introduction of applicator into the rectum causes additional pain

IF PREGNANT OR BREAST-FEEDING

ask a health professional before use

KEEP OUT OF REACH OF CHILDREN

If swallowed, get medical help or contact a Poison Control Center right away. (1-800-222-1222)

DIRECTIONS

cleanse the affected area with an appropriate cleansing wipe or clean tissue paper

when fist opening the tube, puncture foil seal with top end of cap

apply to the affected area up to 4 times only, especially at night, in the morning or after each bowel movement

intrarectal use: remove cover from applicator, attach applicator to tube, lubricate applicator after each use and replace cover

also apply ointment to external area

regular use provides continual therapy for relief of symptoms

children under 12 year of age: ask a doctor

OTHER INFORMATION

store at 20 -25°C (68 -77°F)

INACTIVE INGREDIENTS

Coptis Chinensis Root, Petrolatum, Mineral Oil, Stearic Acid, Glyceryl Monostearate, Sodium Dodecylbenzenesulfonate, Cetostearyl Alcohol, Water

QUESTIONS?

Call 1 (626)285-1600 Monday through Friday, 9:00 a.m. to 5:30 p.m. P.S.T